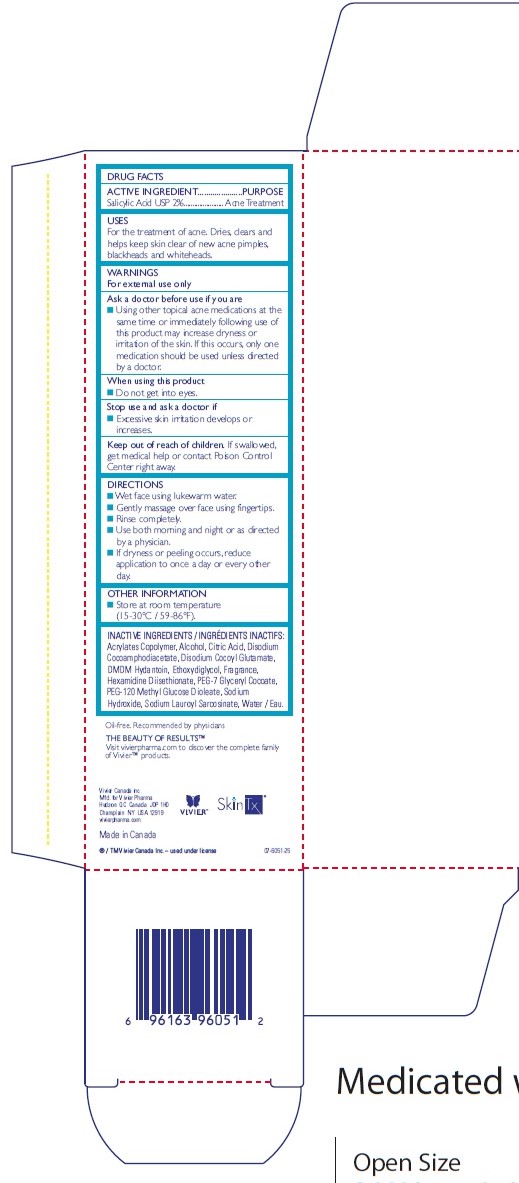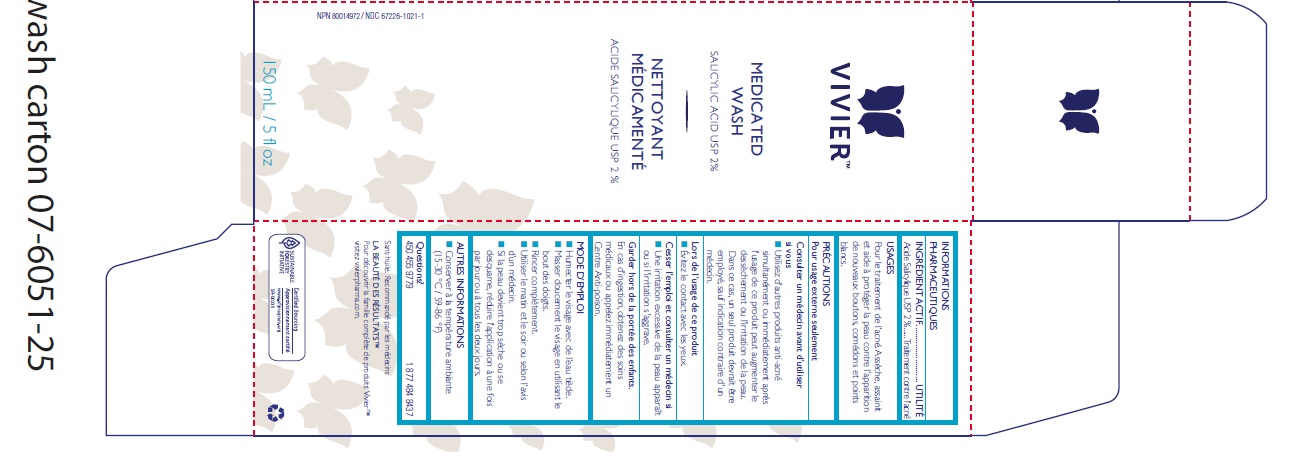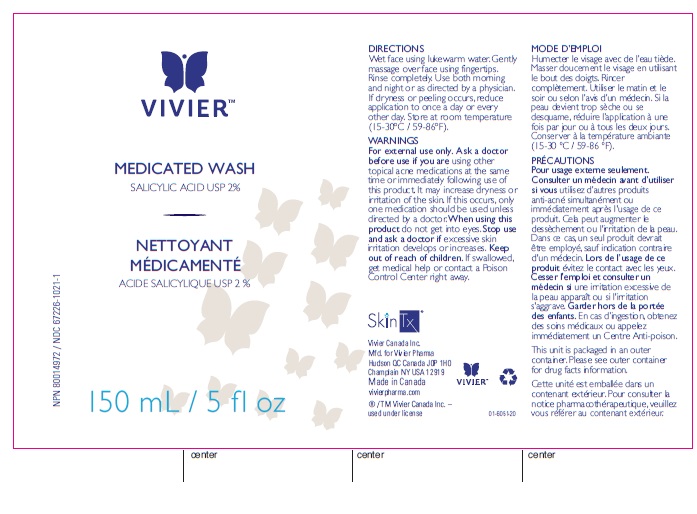 DRUG LABEL: Medicated Wash
NDC: 67226-1021 | Form: LIQUID
Manufacturer: Vivier Pharma, Inc.
Category: otc | Type: HUMAN OTC DRUG LABEL
Date: 20231114

ACTIVE INGREDIENTS: SALICYLIC ACID 20 mg/1 mL
INACTIVE INGREDIENTS: ALCOHOL; CITRIC ACID MONOHYDRATE; DISODIUM COCOAMPHODIACETATE; DISODIUM COCOYL GLUTAMATE; DMDM HYDANTOIN; DIETHYLENE GLYCOL MONOETHYL ETHER; HEXAMIDINE DIISETHIONATE; PEG-7 GLYCERYL COCOATE; PEG-120 METHYL GLUCOSE DIOLEATE; SODIUM HYDROXIDE; SODIUM LAUROYL SARCOSINATE; WATER

Medicated Wash

Active Ingredient

Salicylic Acid USP 2%

Purpose

Acne Treatment

Uses

For the treatment of acne. Dries, clears and helps keep skin clear of new acne pimples, blackheads and white heads.

WARNINGS For exrernal use only

Ask a doctor before use if you are

- Using other topical acne medications at the
  same time or immediately following use of
  this product may increase dryness or
  irritation of the skin. If this occurs, only one
  medication should be used unless directed
  by a doctor

When using this product

- Do not get into eyes.

Stop use and ask a doctor if

- Excessive skin irritation develops or increases.

Keep out of reach of children.

If swallowed, get medical help or contact Poison Control Center right away.

Directions

- Wet face using lukewarm water.
- Gently massage over the face using fingertips.
- Rinse completely.
- Use both morning and night or as directed by a physician.
- If dryness or peeling occurs, reduce application to once a day or every other day.

Other Information

- Store at room temperature
  (15-30°C / 59-86°F).

Inactive Ingredients

Acrylates Copolymer, Alcohol, Citric Acid, Disodium
Cocoamphodiacetate, Disodium Cocoyl Glutamate,
DMDM Hydantoin, Ethoxydiglycol, Fragrance,
Hexamidine Diisethionate, PEG-7 Glyceryl Cocoate,
PEG-120 Methyl Glucose Dioleate, Sodium
Hydroxide, Sodium Lauroyl Sarcosinate, Water / Eau.